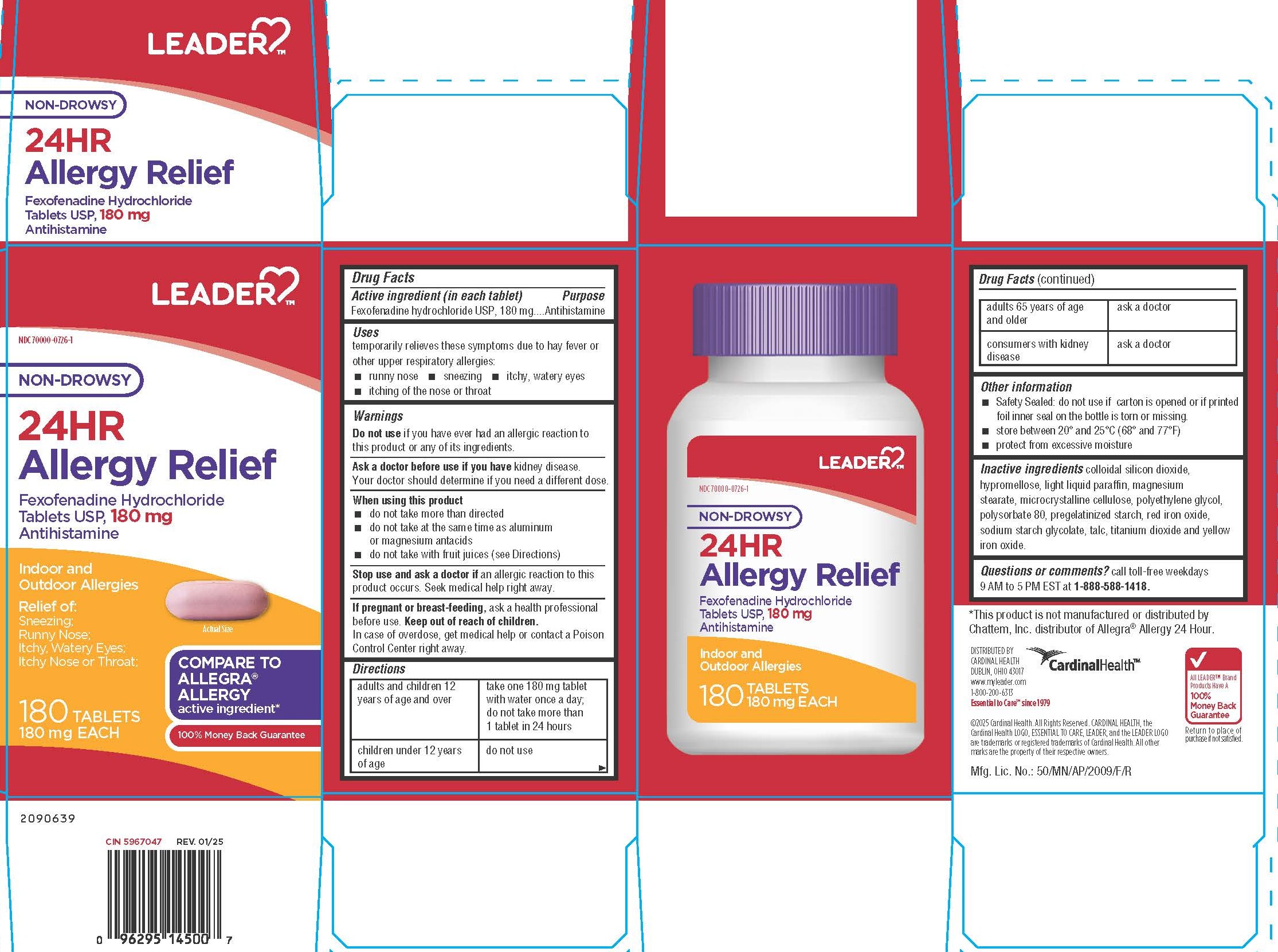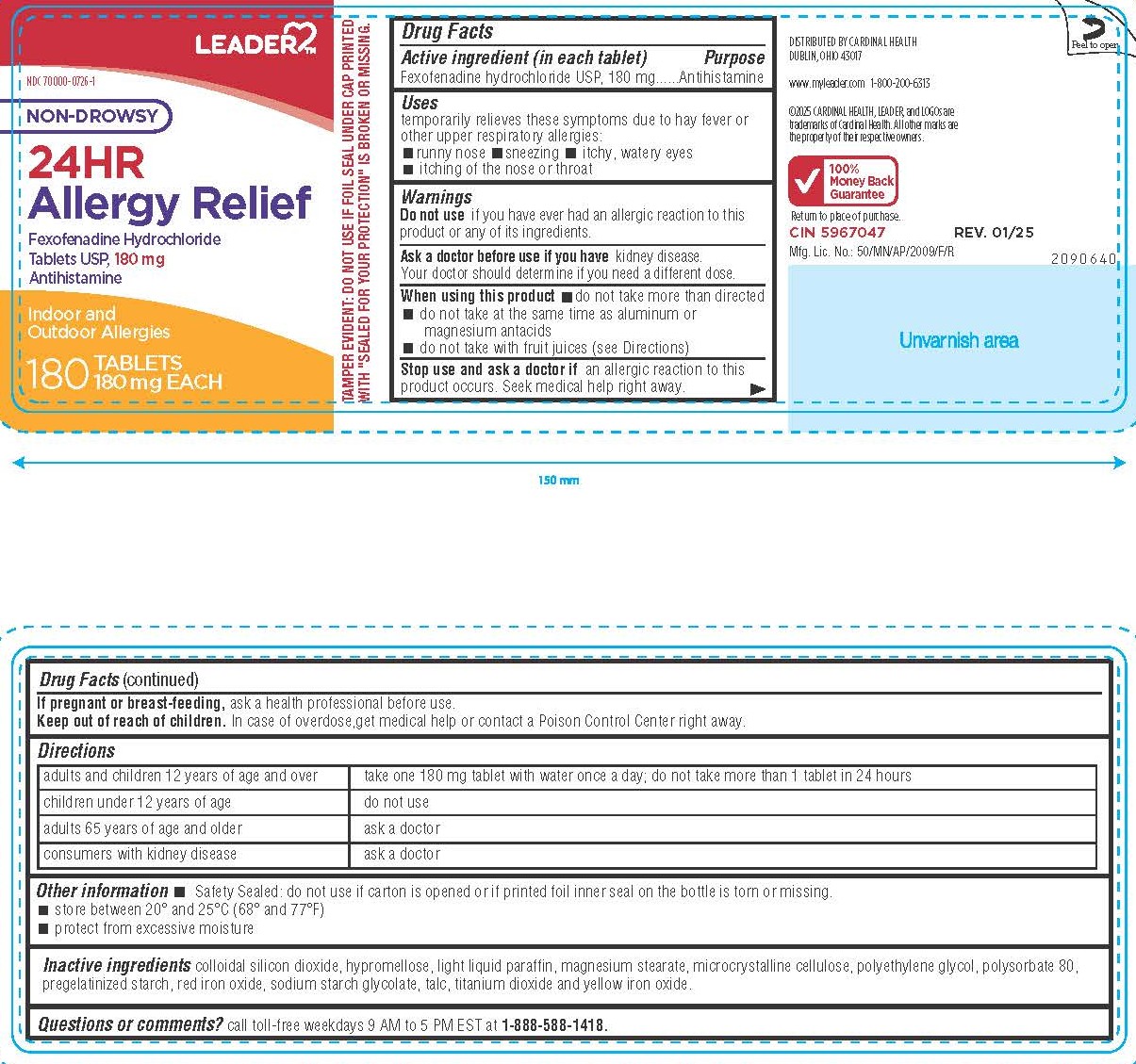 DRUG LABEL: 24HR Allergy Relief
NDC: 70000-0726 | Form: TABLET
Manufacturer: CARDINAL HEALTH 110, LLC. DBA LEADER
Category: otc | Type: HUMAN OTC DRUG LABEL
Date: 20250612

ACTIVE INGREDIENTS: FEXOFENADINE HYDROCHLORIDE 180 mg/1 1
INACTIVE INGREDIENTS: SILICON DIOXIDE; HYPROMELLOSE, UNSPECIFIED; PARAFFIN; MAGNESIUM STEARATE; MICROCRYSTALLINE CELLULOSE; POLYETHYLENE GLYCOL, UNSPECIFIED; POLYSORBATE 80; STARCH, CORN; FERRIC OXIDE RED; SODIUM STARCH GLYCOLATE TYPE A; TALC; TITANIUM DIOXIDE; FERRIC OXIDE YELLOW

LEADER
NON-DROWSY
24HR Allergy Relief
Fexofenadine Hydrochloride Tablets USP
180 mg
Indoor and Outdoor Allergies

Drug Facts Active ingredient (in each tablet)

Fexofenadine Hydrochloride USP, 180 mg

Purpose

Antihistamine

Uses

temporarily relieves these symptoms due to hay fever or other upper respiratory allergies:

- runny nose
- sneezing
- itchy, watery eyes
- itching of the nose or throat

Warnings

Do not use

if you have ever had an allergic reaction to this product or any of its ingredients.

Ask a doctor before use if you have

kidney disease.

Your doctor should determine if you need a different dose.

When using this product

- do not take more than directed
- do not take at the same time as aluminum or magnesium antacids
- do not take with fruit juices (see Directions)

Stop use and ask a doctor if

an allergic reaction to this product occurs. Seek medical help right away.

If pregnant or breast-feeding,

ask a health professional before use.

Keep out of reach of children.

In case of overdose,get medical help or contact a Poison Control Center right away.

Directions

adults and children 12 years of age and over | take one 180mg tablet with water once a day; do not take more than 1 tablet in 24 hours
children under 12 years of age | do not use
adults 65 years of age and older | ask a doctor
consumers with kidney disease | ask a doctor

Other information

- Safety Sealed: do not use if carton is opened or if printed foil inner seal on the bottle is torn or missing.
- store between 20° and 25°C (68° and 77°F)
- protect from excessive moisture

Inactive ingredients

colloidal silicon dioxide, hypromellose, light liquid paraffin, magnesium stearate, microcrystalline cellulose, polyethylene glycol, polysorbate 80,
pregelatinized starch, red iron oxide, sodium starch glycolate, talc, titanium dioxide and yellow iron oxide.

Questions or comments?

call toll-free weekdays 9 AM to 5 PM EST at 1-888-588-1418.

DISTRIBUTED BY CARDINAL HEALTH
DUBLIN, OHIO 43017
www.myleader.com 1-800-200-6313